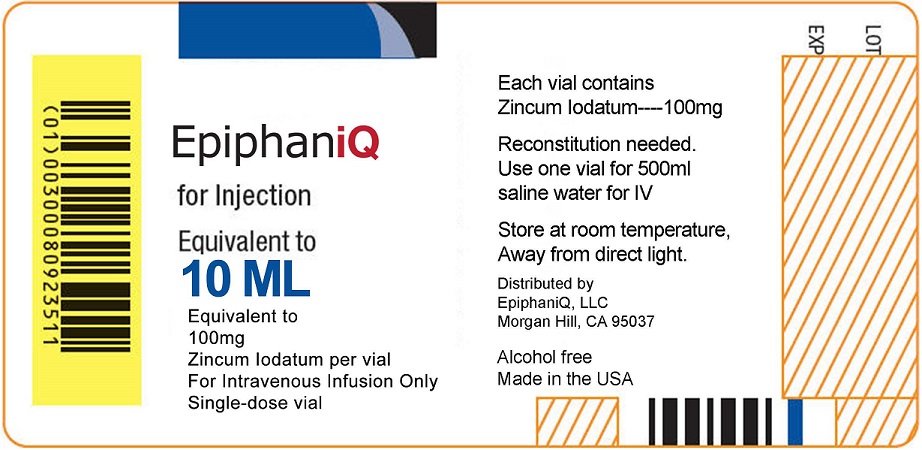 DRUG LABEL: EpiphaniQ
NDC: 79813-301 | Form: INJECTION, SOLUTION, CONCENTRATE
Manufacturer: EpiphaniQ LLC
Category: homeopathic | Type: HUMAN PRESCRIPTION DRUG LABEL
Date: 20211229

ACTIVE INGREDIENTS: ZINC IODIDE 100 mg/10 mL
INACTIVE INGREDIENTS: DIMETHYL SULFOXIDE; WATER

EpiphaniQ for Injection (79813-301)

DIRECTIONS

For Intravenous Infusion Only
Single-dose vial

Each vial contains
Zincum Iodatum----100mg

Reconstitution needed.
Use one vial for 500ml saline water for IV